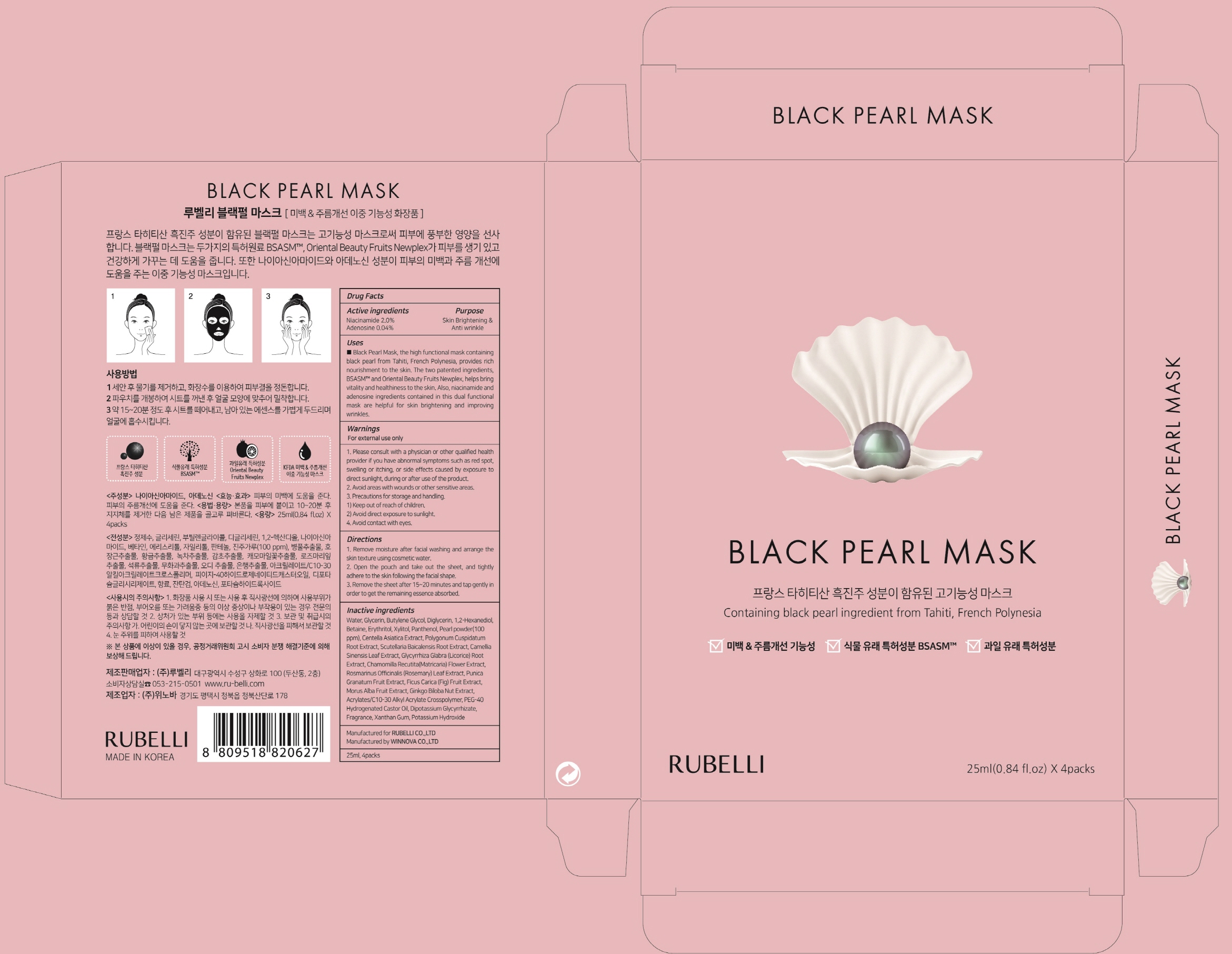 DRUG LABEL: RUBELLI Black Pearl Mask
NDC: 71006-040 | Form: PATCH
Manufacturer: RUBELLI CO.,LTD
Category: otc | Type: HUMAN OTC DRUG LABEL
Date: 20211129

ACTIVE INGREDIENTS: Niacinamide 0.5 g/25 mL; Adenosine 0.01 g/25 mL
INACTIVE INGREDIENTS: Water; Glycerin

ACTIVE INGREDIENT

Active ingredients: Niacinamide 2.0%, Adenosine 0.04%

INACTIVE INGREDIENT

Inactive ingredients: Water, Glycerin, Butylene Glycol, Diglycerin, 1,2-Hexanediol, Betaine, Erythritol, Xylitol, Panthenol, Pearl powder(100ppm), Centella Asiatica Extract, Polygonum Cuspidatum Root Extract, Scutellaria Baicalensis Root Extract, Camellia Sinensis Leaf Extract, Glycyrrhiza Glabra (Licorice) Root Extract, Chamomilla Recutita(Matricaria) Flower Extract, Rosmarinus Officinalis (Rosemary) Leaf Extract, Punica Granatum Fruit Extract, Ficus Carica (Fig) Fruit Extract, Morus Alba Fruit Extract, Ginkgo Biloba Nut Extract, Acrylates/C10-30 Alkyl Acrylate Crosspolymer, PEG-40 Hydrogenated Castor Oil, Dipotassium Glycyrrhizate, Fragrance, Xanthan Gum, Potassium Hydroxide

PURPOSE

Purpose: Skin Brightening & Anti wrinkle

WARNINGS

Warnings: For external use only 1. Please consult with a physician or other qualified health provider if you have abnormal symptoms such as red spot, swelling or itching, or side effects caused by exposure to direct sunlight, during or after use of the product,. 2. Avoid areas with wounds or other sensitive areas 3. Precautions for storage and handling Keep out of reach of children. Avoid direct exposure to sunlight. Avoid contact with eyes.

KEEP OUT OF REACH OF CHILDREN

Uses

Uses: Black Pearl Mask, the high functional mask containing black pearl from Tahiti, French Polynesia, provides rich nourishment to the skin. The two patented ingredients, BSASM™ and Oriental Beauty Fruits Newplex, helps bring vitality and healthiness to the skin. Also, niacinamide and adenosine ingredients contained in this dual functional mask are helpful for skin brightening and improving wrinkles.

Directions

Directions: 1. Remove moisture after facial washing and arrange the skin texture using cosmetic water. 2. Open the pouch and take out the sheet, and tightly adhere to the skin following the facial shape. 3. Remove the sheet after 15~20 minutes and tap gently in order to get the remaining essence absorbed.